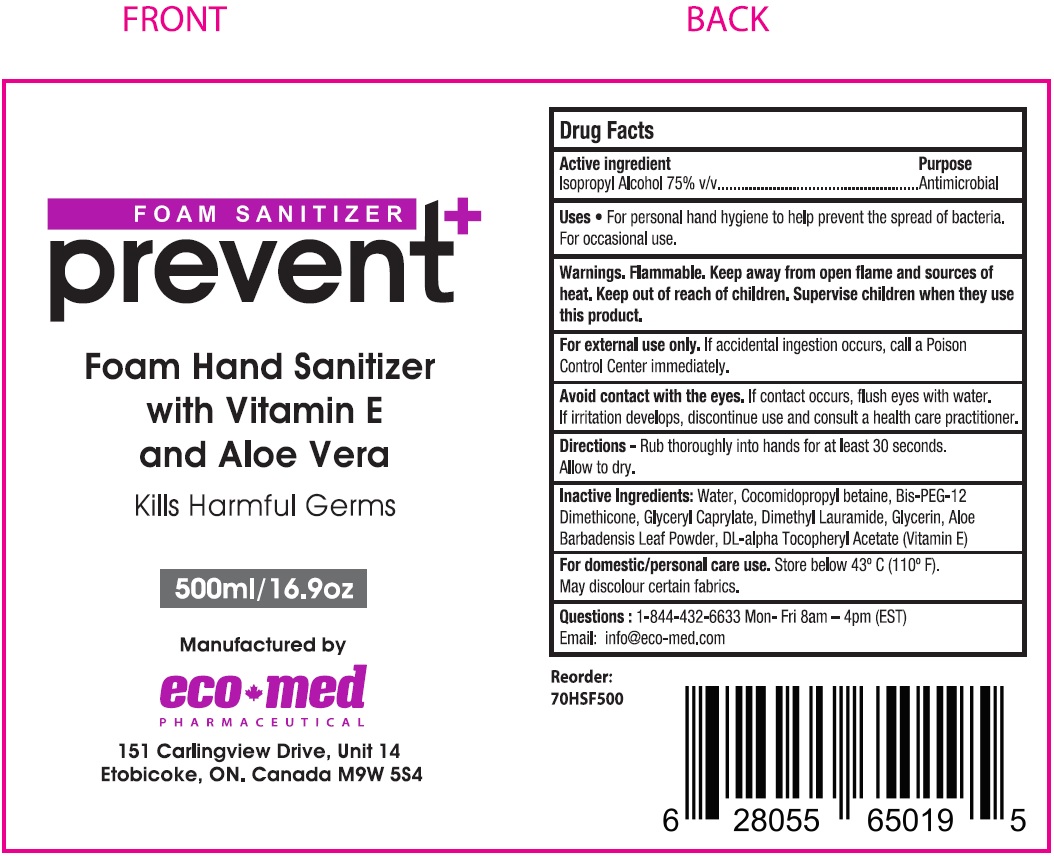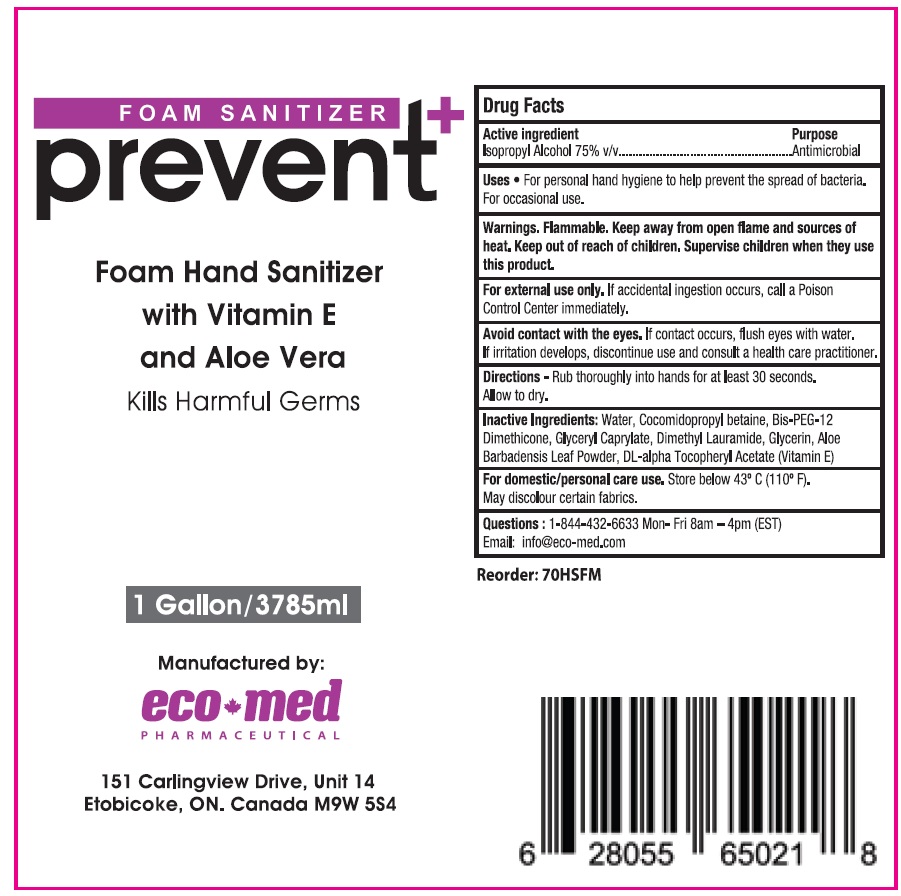 DRUG LABEL: Prevent Foam Sanitizer
NDC: 78835-002 | Form: LIQUID
Manufacturer: Eco-Med Pharmaceuticals, Inc.
Category: otc | Type: HUMAN OTC DRUG LABEL
Date: 20200810

ACTIVE INGREDIENTS: ISOPROPYL ALCOHOL 0.75 mL/1 mL
INACTIVE INGREDIENTS: WATER; COCAMIDOPROPYL BETAINE; GLYCERYL MONOCAPRYLATE; GLYCERIN; ALOE VERA LEAF; .ALPHA.-TOCOPHEROL ACETATE, DL-; N,N-DIMETHYLLAURAMIDE; BIS-PEG-12 DIMETHICONE (70 MPA.S)

Prevent+ Foam Sanitizer

Active ingredient

Isopropyl Alcohol 75% v/v

Purpose

Antimicrobial

Uses

- For personal hand hygiene to help prevent the spread of bacteria. For occasional use.

Warnings.

Flammable. Keep away from open flame and sources of heat

Keep out of reach of children.

Supervise children when they use this product.

For external use only. If accidental ingestion occurs, call a Poison Control Center immediately.

Avoid contact with the eyes. If contact occurs, flush eyes with water. If irritation develops, discontinue use and consult a health care practitioner.

Directions

- Rub thoroughly into hands for at least 30 seconds. Allow to dry.

Inactive Ingredients:

Water, Cocamidopropyl betaine, Bis-PEG-12 Dimethicone, Glyceryl Caprylate, Dimethyl Lauramide, Glycerin, Aloe Barbadensis Leaf Powder, DL-alpha Tocopheryl Acetate (Vitamin E)

For domestic/personal care use.

Store below 43° C (110° F).

May discolour certain fabrics.

Questions :

1-844-432-6633 Mon -Fri 8am - 4pm (EST)

Email: info@eco-med.com